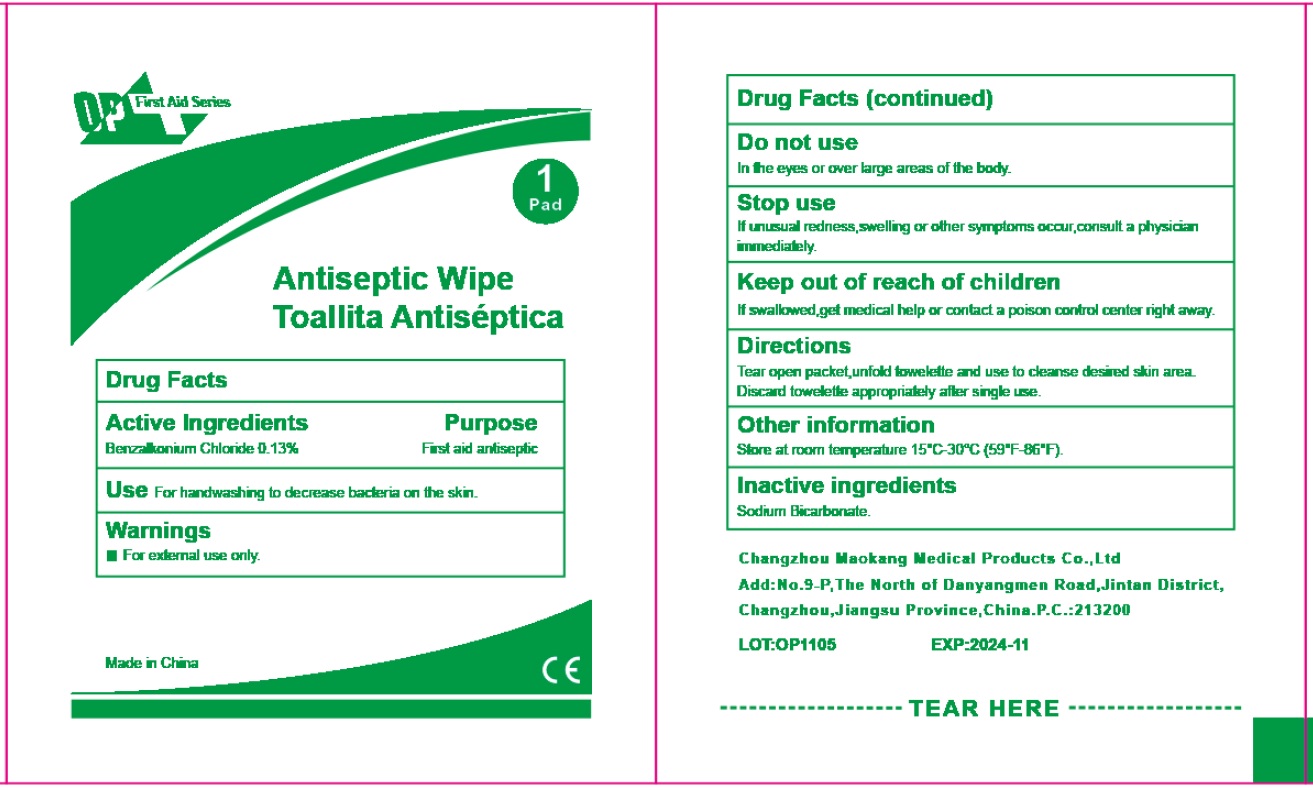 DRUG LABEL: OP First Aid Series Antiseptic Wipe
NDC: 72459-011 | Form: CLOTH
Manufacturer: Yiwu Ori-Power Medtech Co., Ltd.
Category: otc | Type: HUMAN OTC DRUG LABEL
Date: 20260101

ACTIVE INGREDIENTS: BENZALKONIUM CHLORIDE 1.3 mg/1 mL
INACTIVE INGREDIENTS: SODIUM BICARBONATE

OP First Aid Series Antiseptic Wipe

Active Ingredients

Benzalkonium Chloride 0.13%

Purpose

First aid antiseptic

Use

For handwashing to decrease bacteria on the skin.

Warnings

For external use only.

Do not use

In the eyes or over large areas of the body.

Stop use

If unusual redness,swelling or other symptoms occur, consult a physician immediately.

Keep out of reach of children

If swallowed, get medical help or contact a poison control center right away.

Directions

Tear open packet, unfold towelette and use to cleanse desired skin area. Discard towelette appropruately after single use.

Other information

Store at room temperature 15°C-30°C (59°F-86°F).

Inactive ingredients

Sodium Bicarbonate.